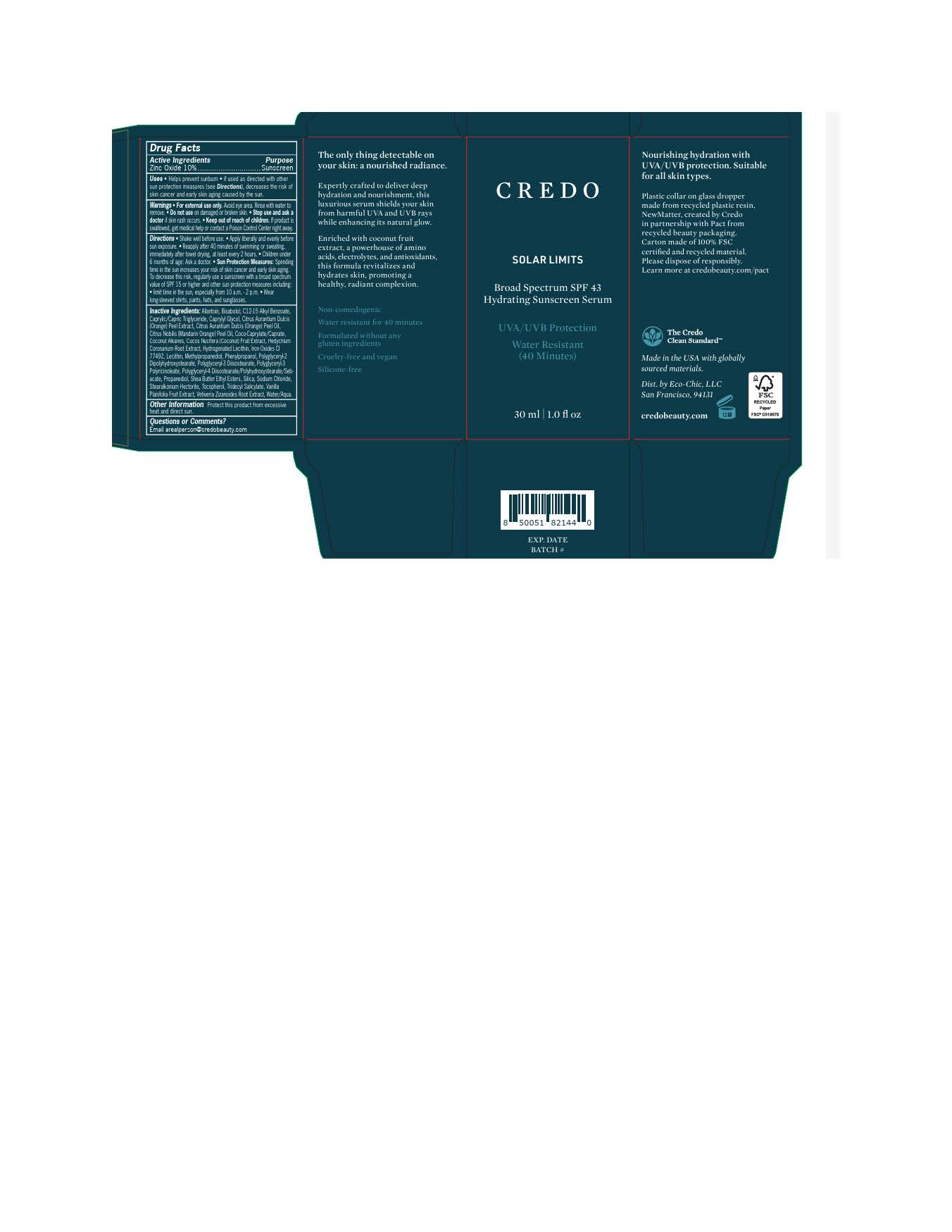 DRUG LABEL: Credo Skin Solar Limits Serum
NDC: 79163-255 | Form: LOTION
Manufacturer: Eco-Chic LLC
Category: otc | Type: HUMAN OTC DRUG LABEL
Date: 20251117

ACTIVE INGREDIENTS: ZINC OXIDE 110 mg/1 mL
INACTIVE INGREDIENTS: COCONUT ALKANES; STEARALKONIUM HECTORITE; POLYGLYCERYL-2 DIPOLYHYDROXYSTEARATE; TOCOPHEROL; FERRIC OXIDE RED; FERRIC OXIDE YELLOW; COCOS NUCIFERA (COCONUT) OIL; TRIDECYL SALICYLATE; CITRUS AURANTIUM DULCIS (ORANGE) PEEL OIL; CITRUS NOBILIS (MANDARIN ORANGE) PEEL OIL; SODIUM CHLORIDE; COCO-CAPRYLATE/CAPRATE; VANILLA PLANIFOLIA FRUIT OIL; FERROSOFERRIC OXIDE; POLYGLYCERYL-4 DIISOSTEARATE/POLYHYDROXYSTEARATE/SEBACATE; LECITHIN, SOYBEAN; ALLANTOIN; SILICON DIOXIDE; .ALPHA.-BISABOLOL, (+)-; WATER; PROPANEDIOL; CAPRYLYL GLYCOL; METHYLPROPANEDIOL; PHENYLPROPANOL; SHEA BUTTER; POLYGLYCERYL-3 DIISOSTEARATE; HEDYCHIUM CORONARIUM ROOT; CAPRYLIC/CAPRIC TRIGLYCERIDE; C12-15 ALKYL BENZOATE; VETIVERIA ZIZANOIDES ROOT OIL

Credo Skin Solar Limits Serum